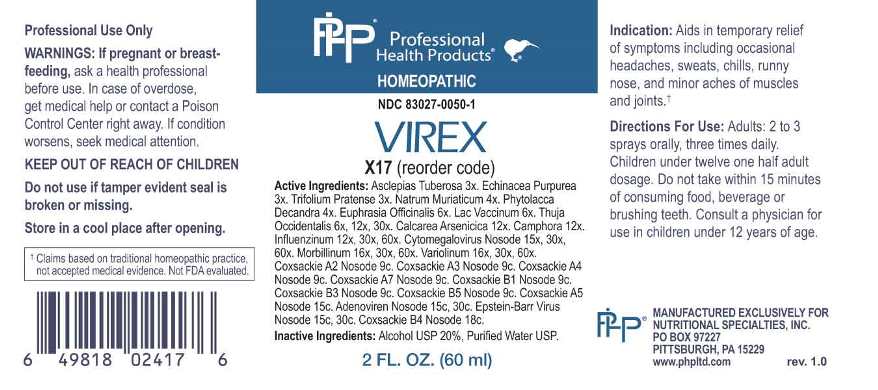 DRUG LABEL: Virex
NDC: 83027-0050 | Form: SPRAY
Manufacturer: Nutritional Specialties, Inc.
Category: homeopathic | Type: HUMAN OTC DRUG LABEL
Date: 20250521

ACTIVE INGREDIENTS: ASCLEPIAS TUBEROSA ROOT 3 [hp_X]/1 mL; ECHINACEA PURPUREA WHOLE 3 [hp_X]/1 mL; TRIFOLIUM PRATENSE FLOWER 3 [hp_X]/1 mL; SODIUM CHLORIDE 4 [hp_X]/1 mL; PHYTOLACCA AMERICANA ROOT 4 [hp_X]/1 mL; EUPHRASIA STRICTA 6 [hp_X]/1 mL; COW MILK 6 [hp_X]/1 mL; THUJA OCCIDENTALIS LEAFY TWIG 6 [hp_X]/1 mL; CALCIUM ARSENATE 12 [hp_X]/1 mL; CAMPHOR (NATURAL) 12 [hp_X]/1 mL; INFLUENZA A VIRUS A/VICTORIA/2570/2019 IVR-215 (H1N1) ANTIGEN (UV, FORMALDEHYDE INACTIVATED) 12 [hp_X]/1 mL; INFLUENZA A VIRUS A/DARWIN/9/2021 IVR-228 (H3N2) ANTIGEN (UV, FORMALDEHYDE INACTIVATED) 12 [hp_X]/1 mL; INFLUENZA B VIRUS B/AUSTRIA/1359417/2021 BVR-26 ANTIGEN (UV, FORMALDEHYDE INACTIVATED) 12 [hp_X]/1 mL; INFLUENZA B VIRUS B/PHUKET/3073/2013 ANTIGEN (UV, FORMALDEHYDE INACTIVATED) 12 [hp_X]/1 mL; HUMAN HERPESVIRUS 5 15 [hp_X]/1 mL; MEASLES VIRUS 16 [hp_X]/1 mL; VARIOLA VIRUS 16 [hp_X]/1 mL; HUMAN COXSACKIEVIRUS A2 9 [hp_C]/1 mL; HUMAN COXSACKIEVIRUS A 9 [hp_C]/1 mL; HUMAN COXSACKIEVIRUS A7 9 [hp_C]/1 mL; HUMAN COXSACKIEVIRUS B1 9 [hp_C]/1 mL; HUMAN COXSACKIEVIRUS B3 9 [hp_C]/1 mL; HUMAN COXSACKIEVIRUS B5 9 [hp_C]/1 mL; HUMAN ADENOVIRUS E SEROTYPE 4 STRAIN CL-68578 ANTIGEN 15 [hp_C]/1 mL; HUMAN HERPESVIRUS 4 15 [hp_C]/1 mL; HUMAN COXSACKIEVIRUS B 18 [hp_C]/1 mL
INACTIVE INGREDIENTS: WATER; ALCOHOL

DRUG FACTS:

ACTIVE INGREDIENTS:

Asclepias Tuberosa 3X, Echinacea Purpurea 3X, Trifolium Pratense 3X, Natrum Muriaticum 4X, Phytolacca Decandra 4X, Euphrasia Officinalis 6X, Lac Vaccinum 6X, Thuja Occidentalis 6X, 12X, 30X, Calcarea Arsenicica 12X, Camphora 12X, Influenzinum 12X, 30X, 60X, Cytomegalovirus Nosode 15X, 30X, 60X, Morbillinum 16X, 30X, 60X, Variolinum 16X, 30X, 60X, Coxsackie A2 Nosode 9C, Coxsackie A3 Nosode 9C, Coxsackie A4 Nosode 9C, Coxsackie A7 Nosode 9C, Coxsackie B1 Nosode 9C, Coxsackie B3 Nosode 9C, Coxsackie B5 Nosode 9C, Coxsackie A5 Nosode 15C, Adenoviren Nosode 15C, 30C, Epstein-Barr Virus Nosode 15C, 30C, Coxsackie B4 Nosode 18C.

PURPOSE:

Aids in temporary relief of symptoms including occasional headaches, sweats, chills, runny nose, and minor aches of muscles and joints.†

†Claims based on traditional homeopathic practice, not accepted medical evidence. Not FDA evaluated.

WARNINGS:

Professional Use Only

If pregnant or breast-feeding, ask a health professional before use.

In case of overdose, get medical help or contact a Poison Control Center right away.

If condition worsens, seek medical attention.

KEEP OUT OF REACH OF CHILDREN

Do not use if tamper evident seal is broken or missing.

Store in a cool place after opening

KEEP OUT OF REACH OF CHILDREN:

In case of overdose, get medical help or contact a Poison Control Center right away.

DIRECTIONS:

Adults: 2 to 3 sprays orally, three times daily. Children under twelve one half adult dosage. Do not take within 15 minutes of consuming food, beverage or brushing teeth. Consult a physician for use in children under 12 years of age.

INDICATIONS:

Aids in temporary relief of symptoms including occasional headaches, sweats, chills, runny nose, and minor aches of muscles and joints.†

†Claims based on traditional homeopathic practice, not accepted medical evidence. Not FDA evaluated.

INACTIVE INGREDIENTS:

Alcohol USP 20%, Purified Water USP.

QUESTIONS:

MANUFACTURED EXCLUSIVELY FOR

NUTRITIONAL SPECIALTIES, INC.

PO BOX 97227

PITTSBURG, PA 15229

www.phpltd.com

PACKAGE LABEL DISPLAY:

Professional

Health Products

HOMEOPATHIC

NDC 83027-0050-1

VIREX

2 FL. OZ (60 ml)